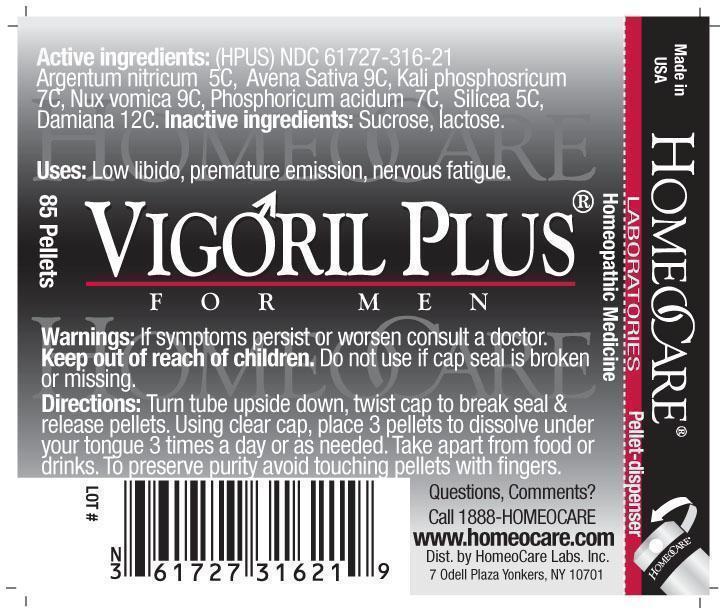 DRUG LABEL: Vigoril Plus
NDC: 61727-316 | Form: PELLET
Manufacturer: Homeocare Laboratories
Category: homeopathic | Type: HUMAN OTC DRUG LABEL
Date: 20210113

ACTIVE INGREDIENTS: SILVER NITRATE 5 [hp_C]/4 g; AVENA SATIVA FLOWERING TOP 9 [hp_C]/4 g; POTASSIUM PHOSPHATE, DIBASIC 7 [hp_C]/4 g; STRYCHNOS NUX-VOMICA SEED 9 [hp_C]/4 g; PHOSPHORIC ACID 7 [hp_C]/4 g; SILICON DIOXIDE 5 [hp_C]/4 g; TURNERA DIFFUSA LEAFY TWIG 12 [hp_C]/4 g
INACTIVE INGREDIENTS: SUCROSE; LACTOSE

Vigoril Plus

Active ingredients:

Argentum nitricum 5C, Avena Sativa 9C, Kali phosphoricum 7C, Nux vomica 9C, Phosphoricum acidum 7C, Silicea 5C, Damiana 12C.

Inactive ingredients:

Sucrose, lactose.

Purpose:

Low libido, premature emission, nervous fatigue.

Keep out of reach of children.

Indications and Usage:

Turn tube upside down, twist cap to break seal & release pellets. Using clear cap, place 3 pellets to dissolve under your tongue 3 times a day or as needed. Take apart from food or drinks. To preserve purity avoid touching pellets with fingers.

Warnings:

If symptoms persist or worsen consult a doctor. Keep out of reach of children. Do not use if cap seal is broken or missing.

Dosage and Administration:

Turn tube upside down, twist cap to break seal & release pellets. Using clear cap, place 3 pellets to dissolve under your tongue 3 times a day or as needed. Take apart from food or drinks. To preserve purity avoid touching pellets with fingers.

Vigoril Plus

Homeopathic Medicine

85 Pellets